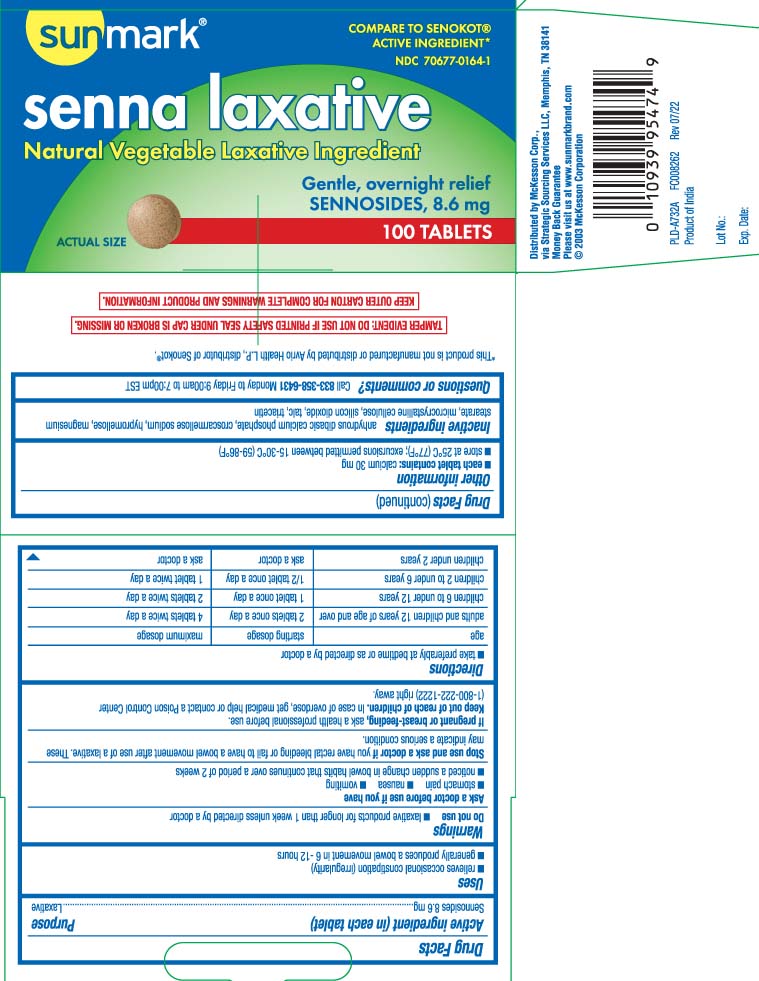 DRUG LABEL: Senna Laxative
NDC: 70677-0164 | Form: TABLET
Manufacturer: Strategic Sourcing Services LLC
Category: otc | Type: HUMAN OTC DRUG LABEL
Date: 20260105

ACTIVE INGREDIENTS: SENNOSIDES 8.6 mg/1 1
INACTIVE INGREDIENTS: CROSCARMELLOSE SODIUM; ANHYDROUS DIBASIC CALCIUM PHOSPHATE; HYPROMELLOSES; MAGNESIUM STEARATE; TALC; CELLULOSE, MICROCRYSTALLINE; TRIACETIN; SILICON DIOXIDE

Drug Facts

Active ingredient (in each tablet)

Sennosides 8.6 mg

Purpose

Laxative

Uses

- relieves occasional constipation (irregularity)
- generally produces bowel movement in 6-12 hours

Warnings

Do not use

- laxative products for longer than 1 week unless directed by a doctor

Ask a doctor before use if you have

- stomach pain
- nausea
- vomiting
- noticed a sudden change in bowel habits that continues over a periodof 2 weeks

Stop use and ask a doctor if

you have rectal bleeding or fail to have a bowel movement after use of a laxative. These may indicate a serious condition.

If pregnant or breast-feeding,

ask a health professional before use.

Keep out of reach of children.

In case of overdose, get medical help or contact a Poison Control Center (1-800-222-1222) right away.

Directions

- take preferably at bedtime or as directed by a doctor

age | starting dosage | maximum dosage
adults and children 12 years of age and over | 2 tablets once a day | 4 tablets twice a day
children 6 to under 12 years | 1 tablet once a day | 2 tablets twice a day
children 2 to under 6 years | 1/2 tablet once a day | 1 tablet twice a day
children under 2 years | ask a doctor | ask a doctor

Other information

- each tablet contains: calcium 30 mg
- store at 25ºC (77ºF); excursions permitted between 15-30ºC (59-86ºF)

Inactive ingredients

croscarmellose sodium, anhydrous dibasic calcium phosphate dihydrate, hypromellose, magnesium stearate, microcrystalline cellulose, silicon dioxide, talc, triacetin

Questions or comments?

Call 1-833-358-6431 Monday to Friday 9:00am to 7:00pm EST

Principal Display Panel

COMPARE TO SENOKOT® ACTIVE INGREDIENT*

Senna laxative

Natural Vegetable Laxative Ingredient

Gently, overnight relief

SENNOSIDES, 8.6 MG

TABLETS

*This product is not manufactured or distributed by Avrio Health L.P., distributor of Senokot®.

TAMPER EVIDENT: DO NOT USE IF PRINTED SAFETY SEAL UNDER CAP IS BROKEN OR MISSING.

KEEP OUTER CARTON FOR COMPLETE WARNINGS AND PRODUCT INFORMATION.

Distributed by McKesson Corp.,

via Strategic Sourcing Services LLC, Memphis, TN 38141

www.sunmarkbrand.com

Product Labeling

SUNMARK Senna Laxative